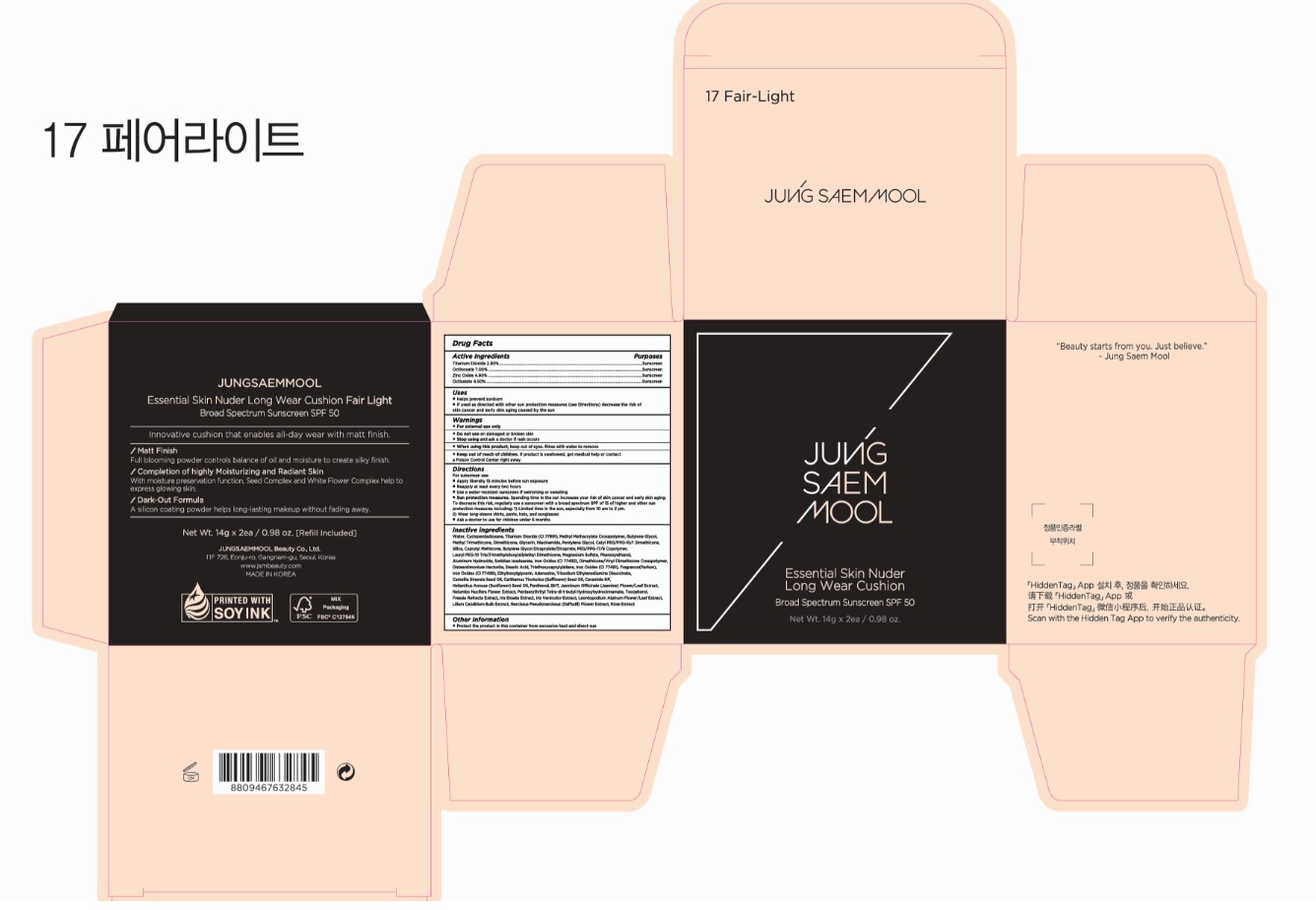 DRUG LABEL: JUNGSAEMMOOL Essential Skin Nuder Longwear Cushion Fair Light
NDC: 71261-035 | Form: CREAM
Manufacturer: Jungsaemmool Beauty Co., Ltd.
Category: otc | Type: HUMAN OTC DRUG LABEL
Date: 20240804

ACTIVE INGREDIENTS: TITANIUM DIOXIDE 29 mg/1 g; OCTINOXATE 70 mg/1 g; ZINC OXIDE 49 mg/1 g; OCTISALATE 45 mg/1 g
INACTIVE INGREDIENTS: WATER; CYCLOMETHICONE 5; BUTYLENE GLYCOL; METHYL TRIMETHICONE; DIMETHICONE, UNSPECIFIED; GLYCERIN; NIACINAMIDE; PENTYLENE GLYCOL; CETYL PEG/PPG-10/1 DIMETHICONE (HLB 4); SILICON DIOXIDE; CAPRYLYL TRISILOXANE; BUTYLENE GLYCOL DICAPRYLATE/DICAPRATE; PEG/PPG-17/6 COPOLYMER; MAGNESIUM SULFATE, UNSPECIFIED FORM; PHENOXYETHANOL; ALUMINUM HYDROXIDE; SORBITAN ISOSTEARATE; FERRIC OXIDE YELLOW; DIMETHICONE/VINYL DIMETHICONE CROSSPOLYMER (HARD PARTICLE); DISTEARDIMONIUM HECTORITE; STEARIC ACID; TRIETHOXYCAPRYLYLSILANE; FERRIC OXIDE RED; FERROSOFERRIC OXIDE; ETHYLHEXYLGLYCERIN; ADENOSINE; TRISODIUM ETHYLENEDIAMINE DISUCCINATE; CAMELLIA SINENSIS SEED OIL; SAFFLOWER OIL; CERAMIDE NP; SUNFLOWER OIL; PANTHENOL; BUTYLATED HYDROXYTOLUENE; JASMINUM OFFICINALE FLOWER; NELUMBO NUCIFERA FLOWER; PENTAERYTHRITOL TETRAKIS(3-(3,5-DI-TERT-BUTYL-4-HYDROXYPHENYL)PROPIONATE); TOCOPHEROL; LEONTOPODIUM NIVALE SUBSP. ALPINUM FLOWERING TOP; LILIUM CANDIDUM BULB; NARCISSUS PSEUDONARCISSUS FLOWER

71261-035_JUNGSAEMMOOL Essential Skin Nuder Longwear Cushion Fair Light

ACTIVE INGREDIENT

Titanium Dioxide 2.90%
Octinoxate 7.00%

Zinc Oxide 4.90%
Octisalate 4.50%

PURPOSE

Sunscreen

INDICATIONS AND USAGE

Helps prevent sunburn
If used as directed with other sun protection measures (see Directions) decrease the risk of skin cancer and early skin aging caused by the sun

DOSAGE AND ADMINISTRATION

For sunscreen use:
Apply liberally 15 minutes before sun exposure

Reapply at least every two hours
Use a water-resistant sunscreen if swimming or sweating
Sun protection measures. Spending time in the sun increases your risk of skin cancer and early skin aging. To decrease this risk, regularly use a sunscreen with a broad spectrum SPF of 15 of higher and other sun protection measures including: 1) Limited time in the sun, especially from 10 am to 2 pm. 2) Wear long-sleeve shirts, pants, hats, and sunglasses

Ask a doctor to use for children under 6 months

WARNINGS

For external use only

Do not use on damaged or broken skin

When using this product, keep out of eyes. Rinse with water to remove.

Stop using and ask a doctor if rash occurs.

KEEP OUT OF REACH OF CHILDREN

Keep out of reach of the children. If product is swallowed, get medical help or contact a poison control center right away.

INACTIVE INGREDIENT

Water, Cyclopentasiloxane, Titanium Dioxide (CI 77891), Methyl Methacrylate Crosspolymer, Butylene Glycol, Methyl Trimethicone, Dimethicone, Glycerin, Niacinamide, Pentylene Glycol, Cetyl PEG/PPG-10/1 Dimethicone, Silica, Caprylyl Methicone, Butylene Glycol Dicaprylate/Dicaprate, PEG/PPG-17/6 Copolymer, Lauryl PEG-10 Tris(Trimethylsiloxy)silylethyl Dimethicone, Magnesium Sulfate, Phenoxyethanol, Aluminum Hydroxide, Sorbitan Isostearate, Iron Oxides (CI 77492), Dimethicone/Vinyl Dimethicone Crosspolymer, Disteardimonium Hectorite, Stearic Acid, Triethoxycaprylylsilane, Iron Oxides (CI 77491), Fragrance(Parfum), Iron Oxides (CI 77499), Ethylhexylglycerin, Adenosine, Trisodium Ethylenediamine Disuccinate, Camellia Sinensis Seed Oil, Carthamus Tinctorius (Safflower) Seed Oil, Ceramide NP, Helianthus Annuus (Sunflower) Seed Oil, Panthenol, BHT, Jasminum Officinale (Jasmine) Flower/Leaf Extract, Nelumbo Nucifera Flower Extract, Pentaerythrityl Tetra-di-t-butyl Hydroxyhydrocinnamate, Tocopherol, Freesia Refracta Extract, Iris Ensata Extract, Iris Versicolor Extract, Leontopodium Alpinum Flower/Leaf Extract, Lilium Candidum Bulb Extract, Narcissus Pseudonarcissus (Daffodil) Flower Extract, Rose Extract

OTHER SAFETY INFORMATION

Protect the product in the container from excessive heat and direct sun